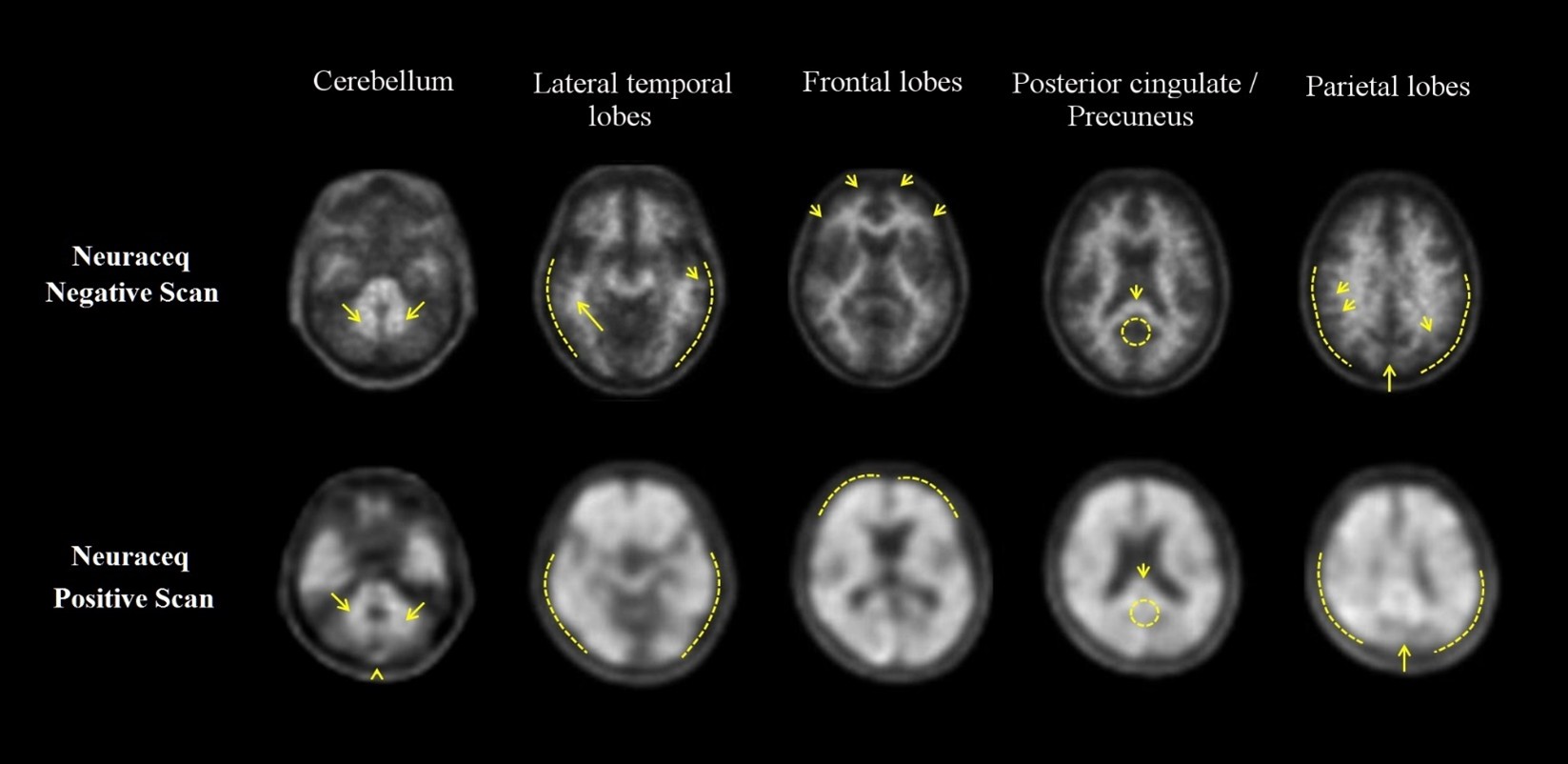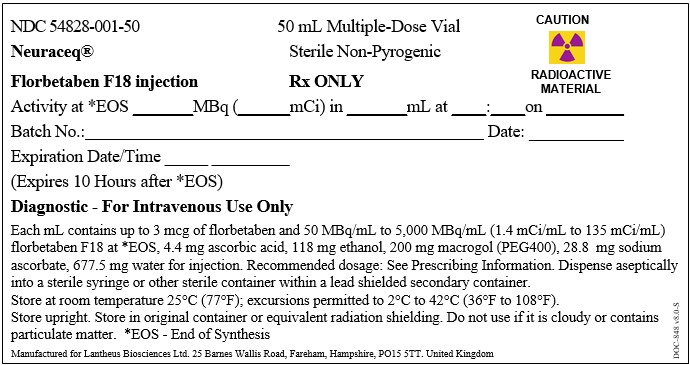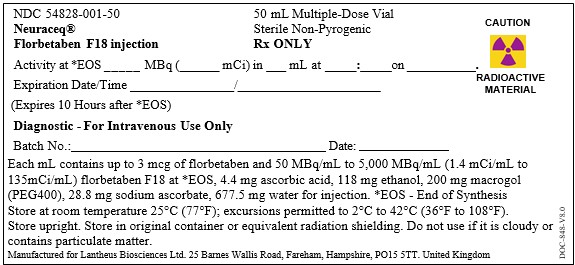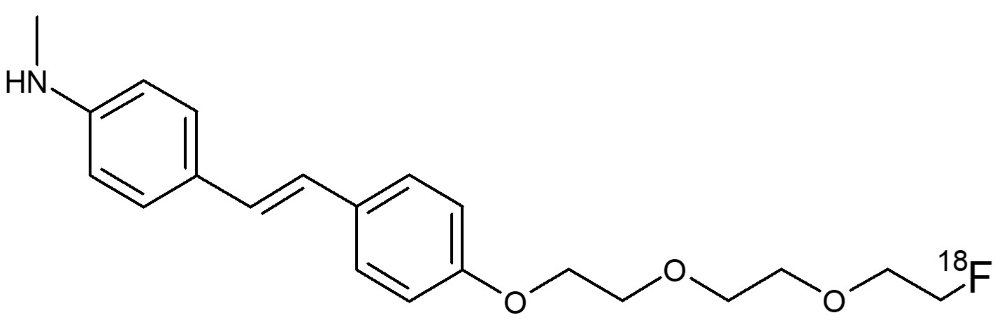 DRUG LABEL: Neuraceq
NDC: 54828-001 | Form: INJECTION, SOLUTION
Manufacturer: Lantheus Biosciences Ltd.
Category: prescription | Type: HUMAN PRESCRIPTION DRUG LABEL
Date: 20260227

ACTIVE INGREDIENTS: FLORBETABEN F-18 135 mCi/1 mL
INACTIVE INGREDIENTS: ALCOHOL 118 mg/1 mL; POLYETHYLENE GLYCOL 400 200 mg/1 mL; ASCORBIC ACID 4.4 mg/1 mL; SODIUM ASCORBATE 28.8 mg/1 mL; WATER 677.5 mg/1 mL

HIGHLIGHTS OF PRESCRIBING INFORMATION

These highlights do not include all the information needed to use NEURACEQ safely and effectively. See full prescribing information for NEURACEQ.
NEURACEQ (florbetaben F 18 injection), for intravenous use
Initial U.S. Approval: 2014

1 INDICATIONS AND USAGE

NEURACEQ is a radioactive diagnostic drug indicated for positron emission tomography (PET) of the brain to estimate amyloid beta neuritic plaque density in adults with cognitive impairment for:

- Evaluation of Alzheimer’s disease (AD) and other causes of cognitive decline
- Selection of patients who are indicated for amyloid beta-directed therapy as described in the prescribing information of the therapeutic products (1)

2 DOSAGE AND ADMINISTRATION

- The recommended amount of radioactivity is 300 MBq (8.1 mCi) administered as a slow single intravenous bolus (6 sec/mL) in a total volume of up to 10 mL. (2.2)
- Follow the injection with an intravenous flush of approximately 10 mL of 0.9% sodium chloride injection. (2.2)
- Obtain 15-minute to 20-minute PET images starting approximately 45 minutes to 130 minutes after drug administration. (2.3)
- See full prescribing information for image interpretation and radiation dosimetry. (2.4, 2.5)

3 DOSAGE FORMS AND STRENGTHS

Injection: 50 MBq/mL to 5,000 MBq/mL (1.4 mCi/mL to 135 mCi/mL) of florbetaben F 18 in up to 50 mL volume at end of synthesis in a multiple-dose vial

4 CONTRAINDICATIONS

None.

5 WARNINGS AND PRECAUTIONS

- Risk of Image Misinterpretation and Other Errors: Image interpretation errors have been observed. (5.1)
- Radiation Risk: NEURACEQ contributes to a patient’s long-term cumulative radiation exposure. Ensure safe drug handling to protect patients and health care providers from unintentional radiation exposure. Advise patients to hydrate before and after administration and to void frequently after administration. (2.1, 2.2, 5.2)

6 ADVERSE REACTIONS

Most common adverse reactions (incidence ≥ 1%) were injection site pain, injection site erythema, and injection site irritation (6.1).

To report SUSPECTED ADVERSE REACTIONS, contact Lantheus Biosciences Ltd. at 1‑833-491-2524 or FDA at 1-800-FDA-1088 or www.fda.gov/medwatch.

8.2 Lactation

Lactation: Temporarily discontinue breastfeeding. A lactating woman should pump and discard breast milk for 24 hours after NEURACEQ administration (8.2).

Recent Major Changes

Indications and Usage (1) 6/2025

Dosage and Administration (2), 6/2025

Image Display and Interpretation (2.4)

FULL PRESCRIBING INFORMATION

1 INDICATIONS AND USAGE

NEURACEQ is indicated for positron emission tomography (PET) of the brain to estimate amyloid beta neuritic plaque density in adults with cognitive impairment for:

- Evaluation of Alzheimer’s disease (AD) and other causes of cognitive decline
- Selection of patients who are indicated for amyloid beta-directed therapy as described in the prescribing information of the therapeutic products

2 DOSAGE AND ADMINISTRATION

2.1 Radiation Safety - Drug Handling

Handle NEURACEQ with appropriate safety measures to minimize radiation exposure during administration [see Warnings and Precautions (5.2)].Use waterproof gloves and effective radiation shielding, including lead-glass syringe shields when handling and administering NEURACEQ.

Radiopharmaceuticals, including NEURACEQ, should be used by or under the control of healthcare providers who are qualified by specific training and experience in the safe use and handling of radionuclides, and whose experience and training have been approved by the appropriate governmental agency authorized to license the use of radionuclides.

2.2 Recommended Dosing and Administration Instructions

Recommended Dosage

The recommended amount of radioactivity of NEURACEQ is 300 MBq (8.1 mCi) in a total volume of up to 10 mL, administered as a single slow intravenous bolus (6 sec/mL). The maximum mass dose is 30 micrograms. Follow the administration with an intravenous flush of approximately 10 mL of 0.9% sodium chloride injection.

Patient Preparation

Instruct patients to hydrate before and after NEURACEQ administration and to void before imaging and frequently thereafter following NEURACEQ administration [see Warnings and Precautions(5.2) ].

Administration

- Use aseptic technique and radiation shielding to withdraw and administer NEURACEQ.
- Visually inspect NEURACEQ for particulate matter and discoloration prior to administration. Do not use NEURACEQ if it contains particulate matter or if it is discolored.
- Do not dilute NEURACEQ.
- Measure the activity of NEURACEQ with a dose calibrator immediately prior to injection.
- Verify patency of the indwelling catheter by a test flush with 0.9% sodium chloride injection prior to administration of NEURACEQ.
- Dispose of unused product in a safe manner in compliance with applicable regulations

2.3 Image Acquisition Guideline

- Position the patient supine with the head positioned to center the brain, including the cerebellum, in the PET scanner field of view. Tape or other flexible head restraints may be employed to reduce head movement.
- Acquire 15-minute to 20-minute PET images starting 45 minutes to 130 minutes after NEURACEQ administration.
- Image reconstruction should include attenuation correction with resulting transaxial pixel sizes between 2 mm and 3 mm.

2.4 Image Display and Interpretation

Image Display

- Display images in the transaxial orientation using gray scale or inverse gray scale. The sagittal and coronal planes may be used for additional orientation purposes.
- CT or MR images may be helpful for anatomic reference purposes. However, visual assessment should be performed using the axial planes according to the recommended reading methodology.
- Locate regions which ‘anatomically’ correspond to white matter structures (e.g., the cerebellar white matter or the splenium) for orientation.
- Review images in a systematic manner, starting with the cerebellum and scrolling up through the lateral temporal and frontal lobes, the posterior cingulate cortex/precuneus, and the parietal lobes.

Visual Assessment

NEURACEQ images should be interpreted only by readers who successfully complete training provided by the manufacturer. The reader training can be accessed here: https://www.neuraceqreadertraining.com/learn.

Perform image interpretation independently of the patient’s clinical features, relying on the recognition of unique image features.

Interpret NEURACEQ images based upon the distribution of signal intensity within the cerebral cortex by comparing the signal intensity in the cortical gray matter and the adjacent white matter. Signal intensity in the gray matter is assessed in the following four brain regions: the temporal lobes, the frontal lobes, the posterior cingulate cortex/precuneus, and the parietal lobes. For a gray matter cortical region to be assessed as showing increased signal, the majority of slices from the respective region must be affected. The signal intensity in the cerebellum does not contribute to the scan interpretation. For example, a positive scan may show retained cerebellar gray-white contrast even when the cortical gray-white contrast is lost.

Some scans may be difficult to interpret due to image noise, atrophy with a thinned cortex, or image blur. If co-registered computerized tomography (CT) or magnetic resonance (MR) images are available, the CT/MR images may be used to clarify the relationship of the NEURACEQ uptake and the gray matter anatomy [see Warnings and Precautions (5.1)].

Negative NEURACEQ Scan

Signal intensity in gray matter is lower than in white matter in all four brain regions (no amyloid beta deposition).

A negative scan indicates sparse to no amyloid beta neuritic plaques. In patients being evaluated for AD and other causes of cognitive decline who have not been treated with amyloid beta-directed therapy, a negative scan is inconsistent with a neuropathological diagnosis of AD at the time of image acquisition and reduces the likelihood that a patient’s cognitive impairment is due to AD. A negative scan result does not preclude the accumulation of amyloid beta in the brain in the future.

Positive NEURACEQ Scan

Smaller area(s) of signal intensity equal to or higher than that present in white matter extending beyond the white matter rim to the outer cortical margin involving the majority of the slices within at least one of the four brain regions (“moderate” amyloid beta deposition), or a large confluent area of signal intensity equal to or higher than that present in white matter extending beyond the white matter rim to the outer cortical margin and involving the entire region including the majority of slices within at least one of the four brain regions (“pronounced” amyloid beta deposition). There is no known clinical or histopathologic correlation distinguishing “moderate” from “pronounced” amyloid beta deposition.

A positive scan establishes the presence of moderate to frequent amyloid beta neuritic plaques. Neuropathological examination has shown that moderate to frequent amyloid beta neuritic plaques are present in patients with AD but may also be present in patients with other types of neurologic conditions as well as older people with normal cognition.

Examples of positive and negative scans for each of the four brain regions are illustrated in Figure 1.

Figure 1 Axial view of negative (top row) and positive (bottom row) Neuraceq PET scans

Cerebellum: A contrast between the white matter (arrows) and gray matter is seen in both negative and positive scans. Extracerebral signal intensity in the scalp and posterior sagittal sinus (arrowhead) can be seen. Lateral temporal lobes:Spiculated or “mountainous” appearance of the white matter (arrows) is seen in the negative scan, and the signal does not reach the outer rim of the brain (dashed line) due to lower signal intensity in the gray matter. The positive scan shows a “plumped”, smooth appearance of the outer border of the brain parenchyma (dashed line) due to signal intensity in the gray matter. Frontal Lobes:Spiculated appearance of the white matter in the frontal lobes (arrows) is seen in the negative scan. The positive scan shows “plumped”, smooth appearance in these regions due to the increased gray matter signal intensity (dashed line). Posterior cingulate/precuneus:Regions adjacent and posterior to the splenium (arrow) appear as a hypo-intense “hole” (circle) in the negative scan, whereas this hole is “filled-up” (circle) in the positive scan. Parietal lobes:In the negative scan, the midline between the parietal lobes can be easily identified (long arrow); white matter has a spiculated appearance (short arrow) with low signal near the outer rim of the brain (dashed line). In the positive scan, the midline between the parietal lobes is much thinner. The cortical areas are “filled-up” and are smooth in appearance as signal intensity extends to the outer rim of the brain.

Quantitative Analysis

Quantification of amyloid beta neuritic plaque levels (e.g., Centiloid scale or standardized uptake value ratio (SUVR)) can be used in conjunction with visual assessment and performed with FDA-authorized software indicated for quantification of brain amyloid beta PET scans. Refer to the drug manufacturer’s training materials for qualitative and quantitative assessment and software manufacturers’ documentation for software operation.

2.5 Radiation Dosimetry

Estimated radiation absorbed doses for adults from intravenous injection of Neuraceq are shown in Table 1.

Table 1 Estimated Radiation Absorbed Doses from Intravenous Injection of Neuraceq
Organ/Tissue | Mean Absorbed Radiation Dose per Unit Administered Activity [microGy/MBq]
Adrenals | 13
Brain | 13
Breasts | 7
Gallbladder Wall | 137
Heart Wall | 14
Kidneys | 24
Liver | 39
Lower Large Intestine-Wall | 35
Lungs | 15
Muscle | 10
Osteogenic Cells | 15
Ovaries | 16
Pancreas | 14
Red Marrow | 12
Skin | 7
Small Intestine | 31
Spleen | 10
Stomach Wall | 12
Testes | 9
Thymus | 9
Thyroid | 8
Upper Large Intestine-Wall | 38
Urinary Bladder Wall | 70
Uterus | 16
Total Body | 11
Effective Dose (microSv/MBq) | 19

The whole-body effective dose resulting from administration of 300 MBq (8.1 mCi) of NEURACEQ in adults is estimated to be 5.8 mSv. When PET/CT is performed, exposure to radiation will increase by an amount dependent on the settings used in the CT acquisition.

3 DOSAGE FORMS AND STRENGTHS

Injection: 50 MBq/mL to 5,000 MBq/mL (1.4 mCi/mL to 135 mCi/mL) of florbetaben F 18 in up to 50 mL volume at end of synthesis (EOS) as a clear solution in a multiple-dose vial.

4 CONTRAINDICATIONS

None

5 WARNINGS AND PRECAUTIONS

5.1 Risk of Image Misinterpretation and Other Errors

Errors may occur in the estimation of brain amyloid beta neuritic plaque density during NEURACEQ image interpretation [ see Clinical Studies (14)].

The use of clinical information in the interpretation of NEURACEQ images has not been evaluated and may lead to an inaccurate assessment. Severe brain atrophy as well as motion artifacts that result in image distortion may limit the ability to distinguish gray and white matter on a NEURACEQ scan.

Perform image interpretation independently of the patient’s clinical information. For cases where there is uncertainty as to the location of cortical signal, use co-registered anatomical imaging to improve localization of signal [see Dosage and Administration (2.4)].

5.2 Radiation Risk

NEURACEQ contributes to a patient's overall long-term cumulative radiation exposure. Long-term cumulative radiation exposure is associated with an increased risk of cancer. Ensure safe drug handling to protect patients and health care providers from unintentional radiation exposure. Advise patients to hydrate before and after administration and to void frequently after administration [see Dosage and Administration (2.1, 2.2)].

6 ADVERSE REACTIONS

6.1 Clinical Trials Experience

Because clinical trials are conducted under widely varying conditions, adverse reaction rates observed in the clinical trials of a drug cannot be directly compared to rates in the clinical trials of another drug and may not reflect the rates observed in clinical practice.

The safety of NEURACEQ was evaluated in 872 adult subjects who received NEURACEQ by intravenous injection in clinical trials. Of these subjects, 724 received a single dose, 78 received two doses, and 70 received three doses at yearly intervals as part of annual repeat scanning. Table 2 shows adverse reactions reported in 1% of these 1,090 administrations from the clinical trials.

Table 2: Adverse Reactions Reported in 1% of NEURACEQ Administrations in Adults in Clinical Trials
Adverse Reaction | NEURACEQ N=1,090 Administrations %
Injection site pain | 3.4
Injection site erythema | 1.7
Injection site irritation | 1.1

8 USE IN SPECIFIC POPULATIONS

8.1 Pregnancy

Risk Summary

There are no available data on NEURACEQ use in pregnant women to evaluate for a drug-associated risk of major birth defects, miscarriage, or adverse maternal or fetal outcomes. Animal reproduction studies have not been conducted with florbetaben F 18 to evaluate its effect on female reproduction and embryo-fetal development.

All radiopharmaceuticals, including NEURACEQ, have the potential to cause fetal harm depending on the stage of fetal development and the magnitude of the radiation dose. If considering NEURACEQ administration to a pregnant woman, inform the patient about the potential for adverse pregnancy outcomes based on the radiation dose from the drug and the gestational timing of exposure.

The background risk of major birth defects and miscarriage for the indicated population is unknown. All pregnancies have a background risk of birth defect, loss, or other adverse outcomes. In the U.S. general population, the estimated background risk of major birth defects and miscarriage in clinically recognized pregnancies is 2% to 4% and 15% to 20%, respectively.

8.2 Lactation

Risk Summary

There are no data on the presence of florbetaben F 18 in human milk, the effects on the breastfed infant, or the effects on milk production. Exposure of NEURACEQ to a breastfed infant can be minimized by temporary discontinuation of breastfeeding (see Clinical Considerations).The developmental and health benefits of breastfeeding should be considered along with the mother's clinical need for NEURACEQ and any potential adverse effects on the breastfed child from NEURACEQ or from the underlying maternal condition.

Clinical Considerations

To decrease radiation exposure to the breastfed infant, advise a lactating woman to pump and discard breast milk for 24 hours after administration of NEURACEQ

8.4 Pediatric Use

The safety and effectiveness of NEURACEQ have not been established in pediatric patients.

8.5 Geriatric Use

Of the 872 subjects in clinical studies of NEURACEQ, 603 (69%) subjects were 65 years of age and older, while 304 (35%) subjects were 75 years of age and older. No overall differences in safety or effectiveness were observed between subjects 65 years of age and older and younger adult subjects.

10 OVERDOSAGE

In the event of administration of a radiation overdose with NEURACEQ, the absorbed organ dose to the patient should be reduced by increasing elimination of the radionuclide from the body by inducing frequent micturition.

11 DESCRIPTION

11.1 Drug Characteristics

NEURACEQ (florbetaben F 18 injection) is a radioactive diagnostic drug for intravenous use.

Chemically, florbetaben F 18 is 4-[(E)-2-(4-{2-[2-(2-[^18F] fluoroethoxy)ethoxy]ethoxy}phenyl)vinyl]-N-methylaniline. The molecular weight is 358.45 and the structural formula is:

NEURACEQ is a sterile, non-pyrogenic, clear solution. Each mL contains up to 3 micrograms of florbetaben and 50 MBq to 5,000 MBq (1.4 mCi to 135 mCi) of florbetaben F 18 at EOS with the following inactive ingredients: 4.4 mg ascorbic acid, 118 mg ethanol, 200 mg macrogol 400, and 28.8 mg sodium ascorbate. The pH of the solution is between 4.5 and 7.

11.2 Nuclear Physical Characteristics

Fluorine-18 (F 18) decays by positron (ß^+) emission to oxygen-18 and has a physical half-life of 109.8 minutes. The principal photons useful for diagnostic imaging are the coincident pair of 511 keV gamma photons, resulting from the interaction of the emitted positron with an electron (Table 3).

Table 3: Principal Radiation Produced from Decay of Fluorine-18
Radiation | Energy Level (keV) | Abundance (%)
Positron | 249.8 | 96.7
Gamma | 511 | 193.4

The point source air-kerma coefficient for F 18 is 3.74E -17 Gy m^2/(Bq s); this coefficient was formerly defined as the specific gamma-ray constant of 5.7 R/hr/mCi at 1 cm. The first half-value thickness of lead for F 18 gamma rays is approximately 6 mm. The relative reduction of radiation emitted by F 18 that results from various thicknesses of lead shielding is shown in Table 4. The use of ~8 cm of lead will decrease the radiation transmission (i.e., exposure) by a factor of about 10,000.

Table 4: Radiation Attenuation of 511 keV by Lead Shielding
Shield Thickness cm of Lead | Coefficient of Attenuation
0.6 | 0.5
2 | 0.1
4 | 0.01
6 | 0.001
8 | 0.0001

For use in correcting for physical decay of this radionuclide, the fractions remaining at selected intervals after calibration are shown in Table 5.

Table 5: Physical Decay Chart for Fluorine-18
Minutes | Fraction Remaining
0 | 1.00
15 | 0.910
30 | 0.828
60 | 0.685
110 | 0.500
220 | 0.250
440 | 0.063

12 CLINICAL PHARMACOLOGY

12.1 Mechanism of Action

Florbetaben F 18 binds to amyloid beta plaques in the brain and the F 18 isotope produces a positron signal that is detected by a PET scanner.^3H-florbetaben in vitro binding experiments revealed two binding sites (Kdof 16 nM and 135 nM) in frontal cortex homogenates from patients with AD. Binding of florbetaben F 18 to amyloid beta plaques in postmortem brain sections from patients with AD using autoradiography correlated with both immunohistochemical and Bielschowsky silver stains. Florbetaben F 18 did not bind to tau or α-synuclein in tissue from patients with AD. Neither florbetaben F 18 nor non-radioactive florbetaben F 19 bound to AT8 positive tau deposited in brain tissue from patients with frontotemporal dementia (FTD), using autoradiography and immunohistochemistry, respectively.

12.2 Pharmacodynamics

Following intravenous administration, florbetaben F 18 crosses the human blood-brain barrier and shows differential retention in brain regions that contain amyloid beta deposits. Differences in signal intensity between brain regions showing specific and non-specific florbetaben F 18 uptake form the basis for the image interpretation method [see Dosage and Administration (2.4)].

12.3 Pharmacokinetics

Following intravenous administration of 300 MBq (8.1 mCi) of NEURACEQ in healthy subjects, approximately 6% of the injected radioactivity was distributed to the brain at 10 minutes post-injection. Florbetaben F 18 plasma concentrations declined by approximately 75% at 20 minutes post-injection, and by approximately 90% at 50 minutes. The F 18 in circulation during the 45-minute to 130-minute imaging window was principally in the form of polar metabolites of florbetaben. Florbetaben F 18 was 98.5% bound to plasma proteins and was eliminated from plasma primarily via the hepatobiliary route with a mean biological half-life of approximately 1 hour.

In vitrostudies show that metabolism of florbetaben is predominantly catalyzed by CYP2J2 and CYP4F2. At 12 hours post-administration, approximately 30% of the injected radioactivity had been excreted in urine. Almost all F 18 radioactivity in urine was excreted as polar metabolites of florbetaben F 18 and only trace amounts of florbetaben F 18 were detected.

In in vitrostudies using human liver microsomes, florbetaben did not inhibit cytochrome P450 enzymes at concentrations present in vivo.

13 NONCLINICAL TOXICOLOGY

13.1 Carcinogenesis, Mutagenesis, Impairment of Fertility

Animal studies have not been performed to evaluate the potential for carcinogenesis, impairment of male or female fertility, or reproductive toxicity by florbetaben F 18.

Mutagenesis

Florbetaben did not demonstrate mutagenic potential in an in vitrobacterial mutation assay (Ames test) using five strains of Salmonella typhimuriumand one strain of Escherichia colior in an in vitrochromosomal aberration assay using human peripheral lymphocytes in the absence and presence of a metabolic activator.

14 CLINICAL STUDIES

14.1 Evaluation of AD and Other Causes of Cognitive Decline

The effectiveness of NEURACEQ was evaluated in two single-arm clinical studies (i.e., Studies 1 and 2) in subjects with a range of cognitive function, including some end-of-life subjects who had agreed to participate in a postmortem brain donation program as well as healthy subjects. Subjects underwent a NEURACEQ injection and scan. Images were interpreted using a clinically applicable binary image interpretation method (negative or positive) by independent readers blinded to all clinical information [see Dosage and Administration (2.4)]. Before image interpretation, all readers underwent either in-person or electronic media training on image interpretation.

The truth standard was based on the histopathologic examination using Bielschowsky silver staining (BSS) of six brain regions assessed by a pathology consensus panel blinded to all clinical information (including PET scan results). NEURACEQ results (negative or positive) were pre-specified to correspond with specific histopathology-derived plaque density scores, based upon a modification of the Consortium to Establish a Registry for Alzheimers Disease (CERAD) criteria, which use neuritic plaque counts as a necessary pathological feature of AD (Table 6). For the subject-level truth standard, if any of the six regions were scored as more than sparse, the subject was classified as positive; if none of the regions were assessed as being more than sparse, the subject was classified as negative.

Table 6: Categorization of Histopathology and NEURACEQ PET Read
Histopathology Categorization |  | NEURACEQ PET Read
Neuritic Plaque Counts | CERAD Score | NEURACEQ PET Read
<1 | None | Negative
1-5 | Sparse | Negative
6-19 | Moderate | Positive
>20 | Frequent | Positive

Study 1 evaluated performance characteristics (sensitivity and specificity) in subjects who died during the study by comparing premortem NEURACEQ PET images to a postmortem truth standard of amyloid beta neuritic plaque density. A total of 205 subjects were dosed with NEURACEQ and imaged. The mean age was 77 years (range 48 to 98 years) and 52% of the subjects were male. By medical history, 137 subjects had AD, 31 had other non-AD dementia, 5 had dementia with Lewy bodies (DLB), and 32 had no clinical evidence of dementia. Among the imaged subjects, 82 subjects died during the study and were included in the primary analysis. The time interval between the NEURACEQ scan and death was less than one year for 45 subjects, between one and two years for 23 subjects, and more than two years for 14 subjects. At autopsy, the subject-level brain amyloid beta neuritic plaque density category was frequent (n = 31), moderate (n = 21), sparse (n = 17), or none (n = 13). Three readers, after undergoing in-person training, interpreted images from the 82 autopsied subjects. Five independent, blinded readers underwent electronic media training and assessed images from the same 82 end-of-life subjects.

Study 2 evaluated inter-reader and intra-reader reproducibility of image interpretation using images from subjects with a truth standard (60 subjects who participated in Study 1) and subjects without a truth standard (50 subjects with mild cognitive impairment (MCI), 139 subjects with AD, 30 subjects with other non-AD dementias/disease, 5 subjects with Parkinsons disease (PD), and 170 healthy subjects). Intra-reader reproducibility was assessed with images from 46 subjects (10%). Among the 454 subjects, the mean age was 71 years (range 22 to 98 years), 193 were females, and 353 were White. Readers underwent electronic media training.

Among subjects who underwent autopsy (n=82; 52 positive and 30 negative based on histopathology), the sensitivity using the majority interpretation of the in-person trained readers (three readers) was 96.2% (95% CI: 86.8%, 99.5%) and specificity was 80.0% (95% CI: 61.4% to 92.3%). The Sensitivity of the readers trained using electronic media (five readers) was 96.2% (95% CI: 86.8%, 99.5%) and specificity was 76.7% (95% CI: 57.7% to 90.1%). The median (and range) of correct, false negative, and false positive reads were 71 (65 to 73), 2 (0 to 5), 7 (6 to 16), respectively, for electronic media training; and were 75 (74, 75), 1 (1, 2), 6 (5, 7), respectively, for in-person training.

Table 7 shows the inter-reader reproducibility for various subject groups in Study 2a. Inter-reader agreement analyses across all five readers showed an overall Fleiss kappa statistic of 0.79 (95% CI: 0.77, 0.83), which met the pre-specified success criterion (95% CI lower bound > 0.60). The percentage of intra-reader agreement for the five readers ranged from 91% to 98%.

Table 7: Inter-Reader Reproducibility of NEURACEQ PET Read Results for Various Subject Groups in Study 2
Subject Group by Cognitive Status and Truth Standard (TS) | Positive; Scans,; nb | Kappa; (95% CI) | Percent of Scans with Inter-Reader Agreement
Subject Group by Cognitive Status and Truth Standard (TS) | Positive; Scans,; nb | Kappa; (95% CI) | 3 of 5 readers agreed | 4 of 5 readers agreed | 5 of 5 readers agreed
All subjects, n=454 | 212 | 0.80 (0.77, 0.83) | 6 | 15 | 78
Subjects with TS, n=60 | 37 | 0.75 (0.67, 0.83) | 10 | 15 | 75
Subjects without TS, n=394 | 175 | 0.80 (0.77, 0.83) | 6 | 15 | 79
AD, n=176; (37 with TS; 139 no TS) | 139 | 0.77 (0.72, 0.81) | 7 | 10 | 83
MCI without TS, n=50 | 28 | 0.84 (0.75, 0.92) | 0 | 20 | 80
Other non-AD dementiac,; n=40; (5 with TS; 35 no TS) | 18 | 0.65 (0.55, 0.74) | 8 | 33 | 60
Healthy subjects, n=188; (18 with TS; 170 no TS) | 26 | 0.55 (0.49, 0.58) | 7 | 15 | 77

aReaders who underwent electronic media training.

bShown is the median number of scans interpreted as positive across the five readers for each group of subjects listed in the first column.

cOther non-AD dementia includes dementia with Lewy bodies (DLB), fronto-temporal lobe dementia, vascular dementia, and dementia associated with Parkinson’s disease (PD).

14.2 Selection of Patients Indicated for Amyloid Beta-Directed Therapy

Refer to the prescribing information of amyloid beta-directed therapy for description of clinical trials in which the efficacy of amyloid beta PET for selecting patients has been established.

Brain amyloid beta PET scans have been used to assess reduction of plaque in some clinical trials of amyloid beta-directed therapies as also described in the prescribing information of the therapeutic products.

16 HOW SUPPLIED/STORAGE AND HANDLING

How Supplied

NEURACEQ (florbetaben F 18 injection) is a clear solution supplied at a concentration of 50 MBq/mL to 5,000 MBq/mL (1.4 mCi/mL to 135 mCi/mL) of florbetaben F 18 in up to 50 mL volume at EOS in a shielded multiple-dose glass vial (NDC 54828-001-50).

Storage and Handling

Store NEURACEQ in the original container with radiation shielding at room temperature 25°C (77°F); excursions permitted to 2°C to 42°C (36°F to 108°F).

NEURACEQ does not contain a preservative.

Do not use after the expiration date and time provided on the container label.

NEURACEQ multiple-dose vial expires 10 hours after EOS.

Dispose of unused product in accordance with all federal, state, and local laws and institutional requirements.

This preparation is for use by persons under license by the Nuclear Regulatory Commission or the relevant regulatory authority of an Agreement State.

17 PATIENT COUNSELING INFORMATION

Radiation Risk

Advise patients of the radiation risk of NEURACEQ. Instruct patients to increase their level of hydration before and after receiving NEURACEQ and to void frequently following administration [see Warnings and Precautions (5.2)].

Pregnancy

Inform pregnant women of the potential risks of fetal exposure to radiation doses with NEURACEQ [see Use in Specific Populations (8.1)].

Lactation

Advise a lactating woman to temporarily discontinue breastfeeding and to pump and discard breast milk for 24 hours after NEURACEQ administration to minimize radiation exposure to the breastfed infant [see Use in Specific Populations (8.2)].

Manufactured for Lantheus Biosciences Ltd.

25 Barnes Wallis Road

Fareham, Hampshire, PO15 5TT.

United Kingdom.

NEURACEQ is a registered trademark of Lantheus Biosciences Ltd.